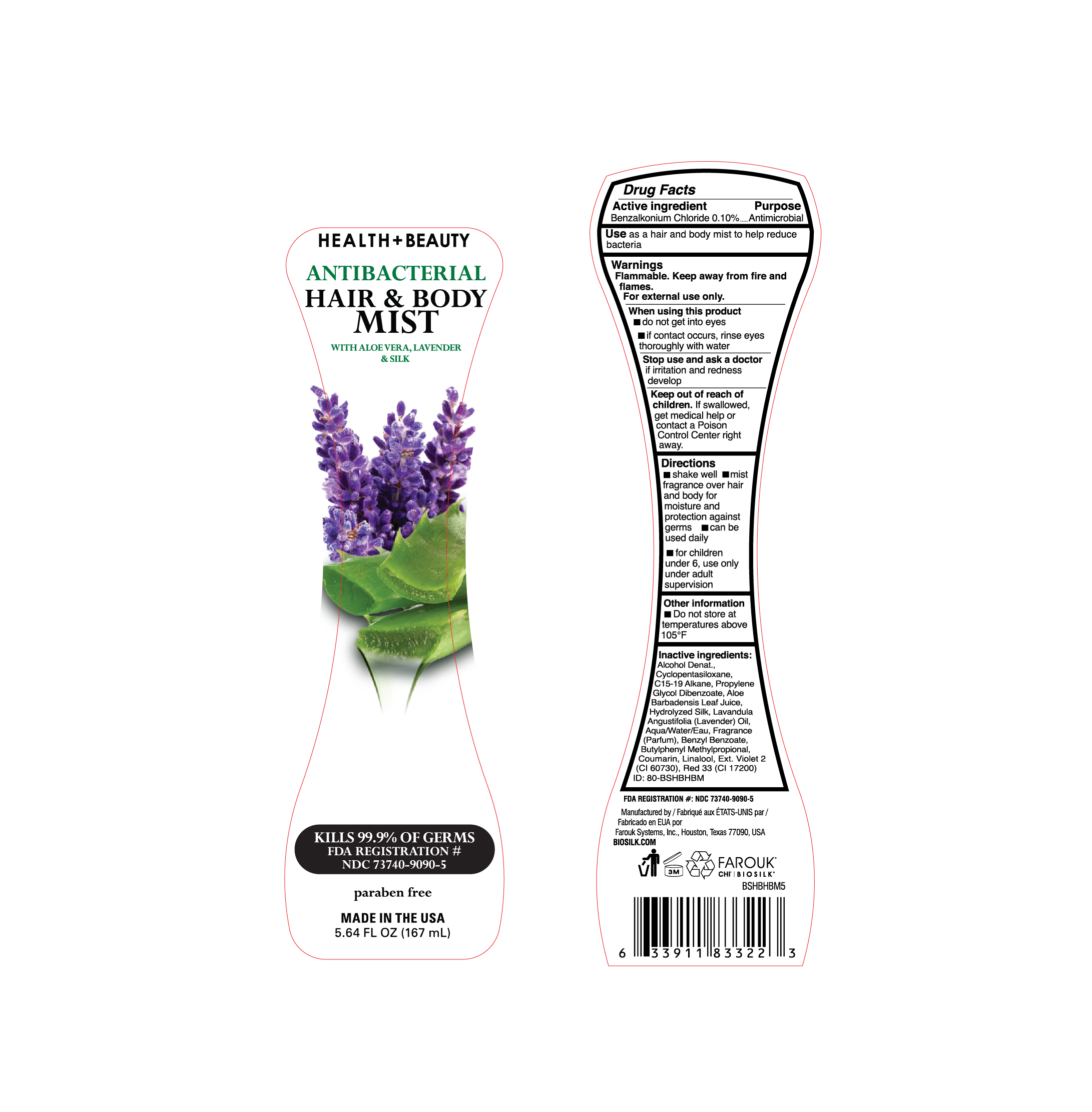 DRUG LABEL: Biosilk Health plus Beauty
NDC: 73740-9090 | Form: SPRAY
Manufacturer: Farouk Systems, Inc.
Category: otc | Type: HUMAN OTC DRUG LABEL
Date: 20201001

ACTIVE INGREDIENTS: BENZALKONIUM CHLORIDE 0.1 g/100 g
INACTIVE INGREDIENTS: WATER 0.099 g/100 g; FRAGRANCE LAVENDER ORC1800979 0.1775 g/100 g; LINALOOL, (+/-)- 0.015 g/100 g; AMINO ACIDS, SILK 0.011 g/100 g; BUTYLPHENYL METHYLPROPIONAL 0.0375 g/100 g; COUMARIN 0.02 g/100 g; C15-19 ALKANE 2 g/100 g; PROPYLENE GLYCOL DIBENZOATE 2 g/100 g; CYCLOMETHICONE 5 20.27952 g/100 g; LAVENDER OIL 0.01 g/100 g; BENZYL BENZOATE 0.25 g/100 g; D&C RED NO. 33 0.00008 g/100 g; ALCOHOL 74.999 g/100 g; ALOE VERA LEAF 0.001 g/100 g; EXT. D&C VIOLET NO. 2 0.0004 g/100 g

BioSilk Health Beauty Antibacterial Hair and Body Mist with Aloe vera Lavender and Silk

Directions

fragrance over hair
and body for
moisture and
protection against
germs can be
used daily

Inactive ingredients:

Alcohol Denat.,
Cyclopentasiloxane,
C15-19 Alkane, Propylene
Glycol Dibenzoate, Aloe
Barbadensis Leaf Juice,
Hydrolyzed Silk, Lavandula
Angustifolia (Lavender) Oil,
Aqua/Water/Eau, Fragrance
(Parfum), Benzyl Benzoate,
Butylphenyl Methylpropional,
Coumarin, Linalool, Ext. Violet 2
(CI 60730), Red 33 (CI 17200)

USE

Use as a hair and body mist to help reduce
bacteria

USE

Use as a hair and body mist to help reduce
bacteria

Active Ingredient

Benzalkonium Chloride 0.10%

Stop use and ask a doctor

if irritation and redness
develop

Keep out of reach of children.

Keep out of reach of
children. If swallowed,
get medical help or
contact a Poison
Control Center right
away.

Stop use and ask a doctor

if irritation and redness
develop

Other information

Do not store at
temperatures above
105°F

Warnings

Flammable. Keep away from fire and
flames.
For external use only.
When using this product
do not get into eyes
if contact occurs, rinse eyes
thoroughly with water

Purpose

Antimicrobial

Biosilk Health +Beauty Antibacterial Hair & Body Mist with aloe vera, lavender & silk

Biosilk Health +Beauty
Antibacterial Hair & Body Mist
with aloe vera, lavender & silk
Kills 99.9% of germs

FDA Registration #

NDC 73740-9090-5

paraben free

Made in the USA

5.64 FL OZ (167 mL)